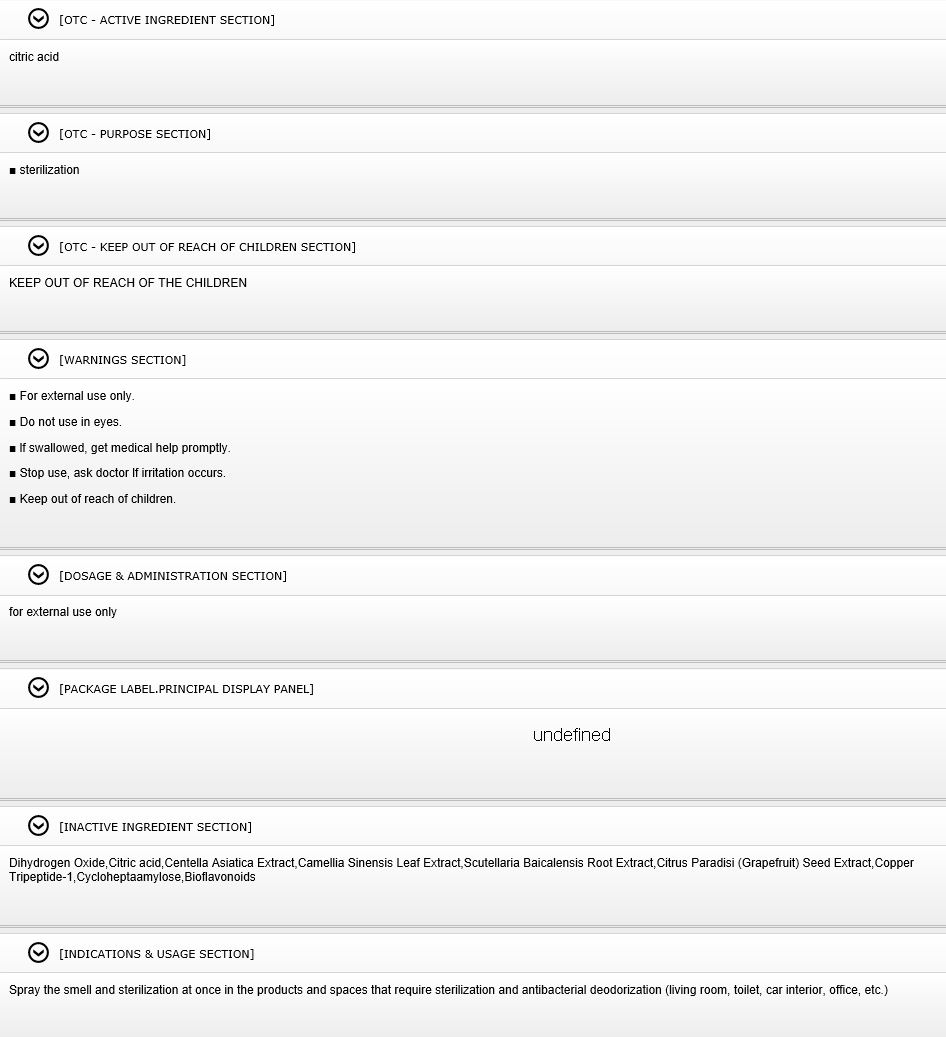 DRUG LABEL: KID-CLEAN Epiguard (Herbage Basis germ Growth InhibitsSolution)
NDC: 78077-0001 | Form: GEL
Manufacturer: KOREA JINTECH
Category: otc | Type: HUMAN OTC DRUG LABEL
Date: 20200523

ACTIVE INGREDIENTS: CITRIC ACID MONOHYDRATE 104 g/100 mL
INACTIVE INGREDIENTS: CENTELLA ASIATICA; CAMELLIA SINENSIS SEED OIL

Drug Facts

ACTIVE INGREDIENT

citric acid

PURPOSE

■ sterilization

KEEP OUT OF REACH OF THE CHILDREN

WARNINGS

■ For external use only.

■ Do not use in eyes.

■ lf swallowed, get medical help promptly.

■ Stop use, ask doctor lf irritation occurs.

■ Keep out of reach of children.

DOSAGE AND ADMINISTRATION

for external use only

INACTIVE INGREDIENT

Dihydrogen Oxide,Citric acid,Centella Asiatica Extract,Camellia Sinensis Leaf Extract,Scutellaria Baicalensis Root Extract,Citrus Paradisi (Grapefruit) Seed Extract,Copper Tripeptide-1,Cycloheptaamylose,Bioflavonoids

INDICATIONS AND USAGE

Spray the smell and sterilization at once in the products and spaces that require sterilization and antibacterial deodorization (living room, toilet, car interior, office, etc.)